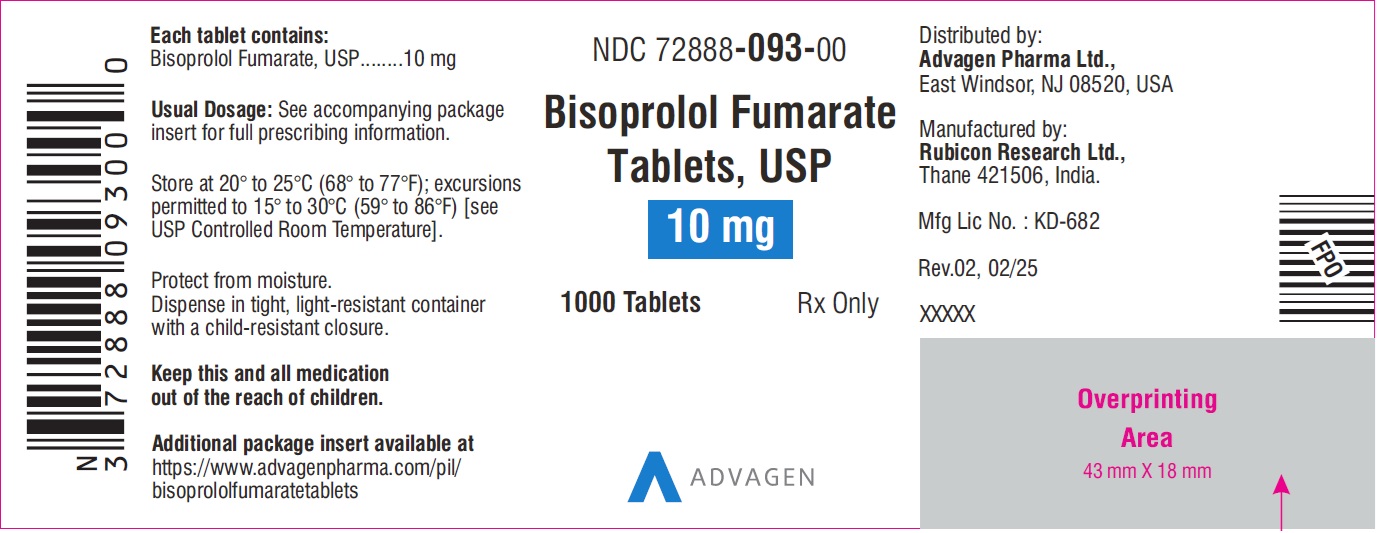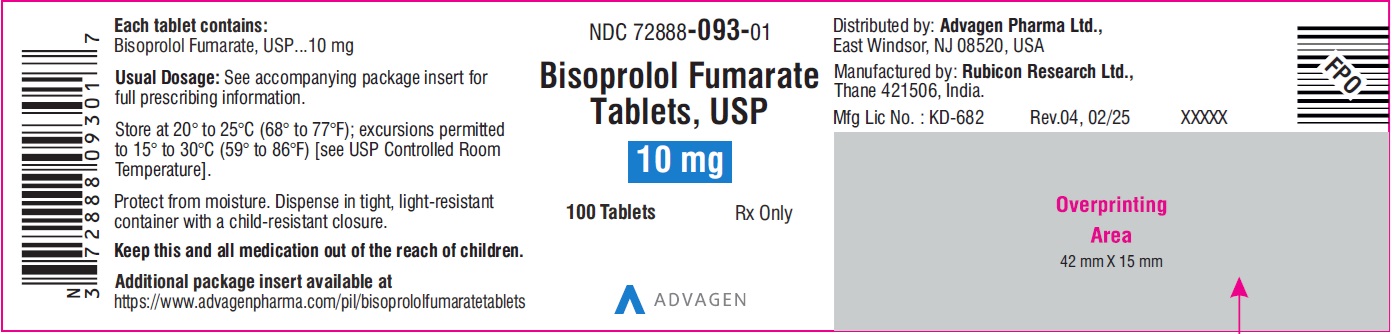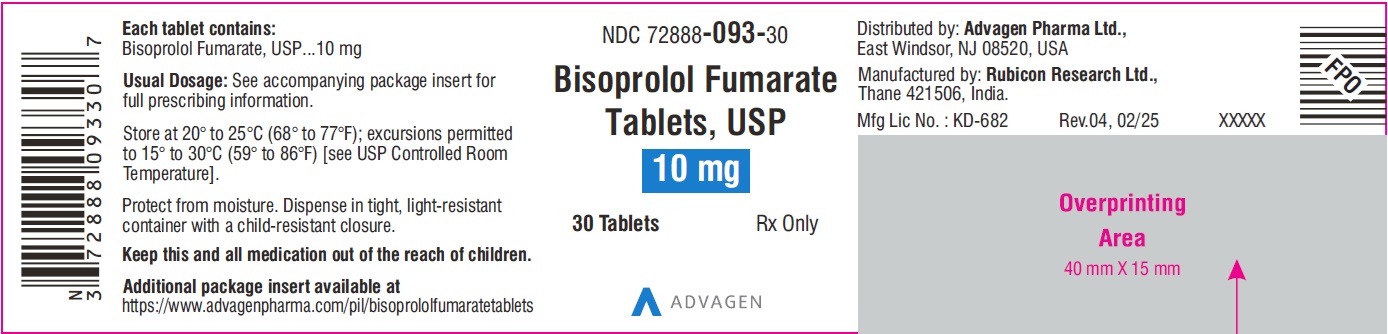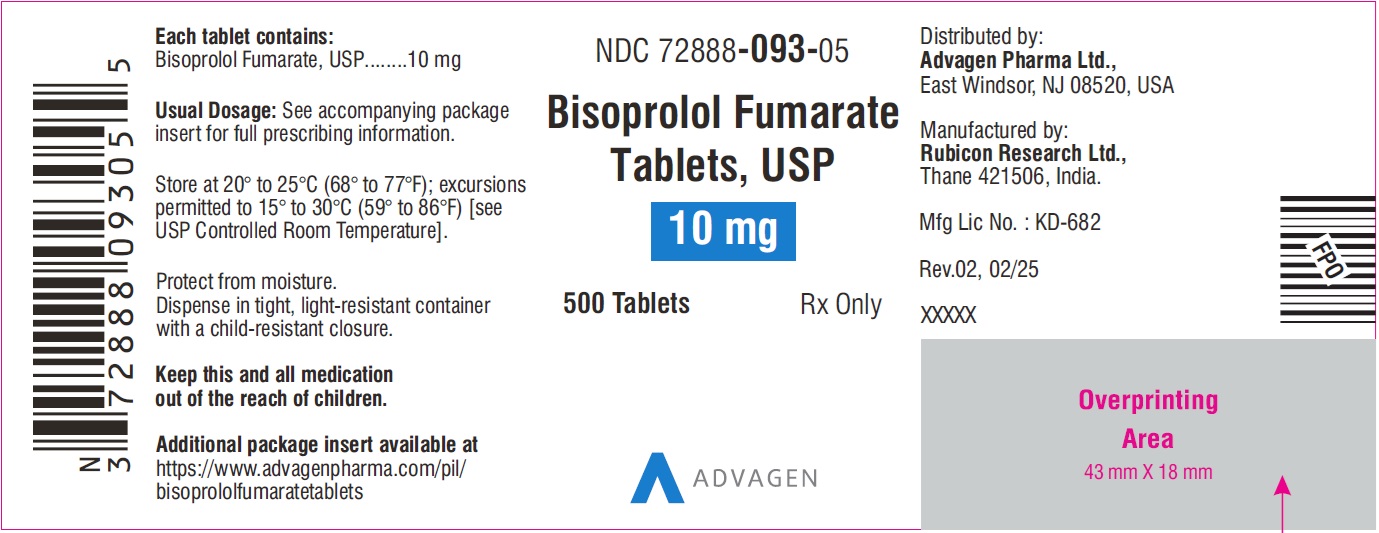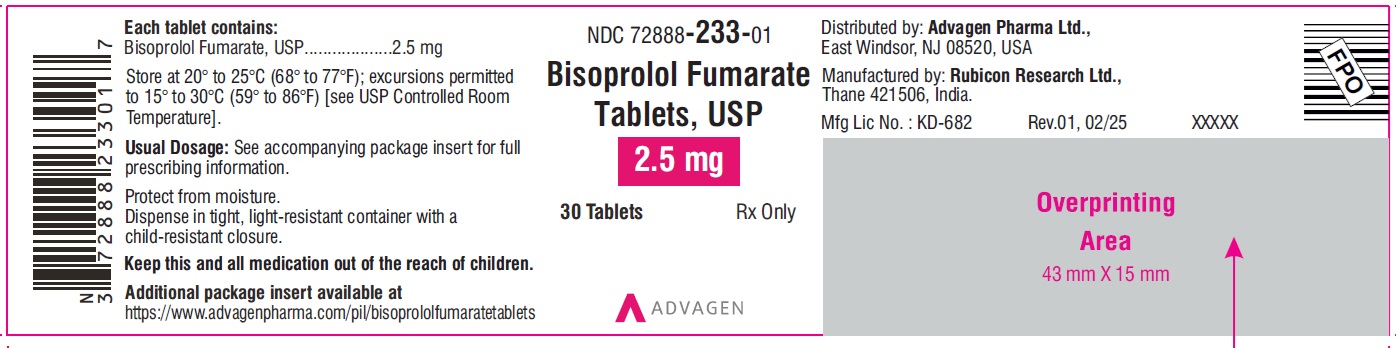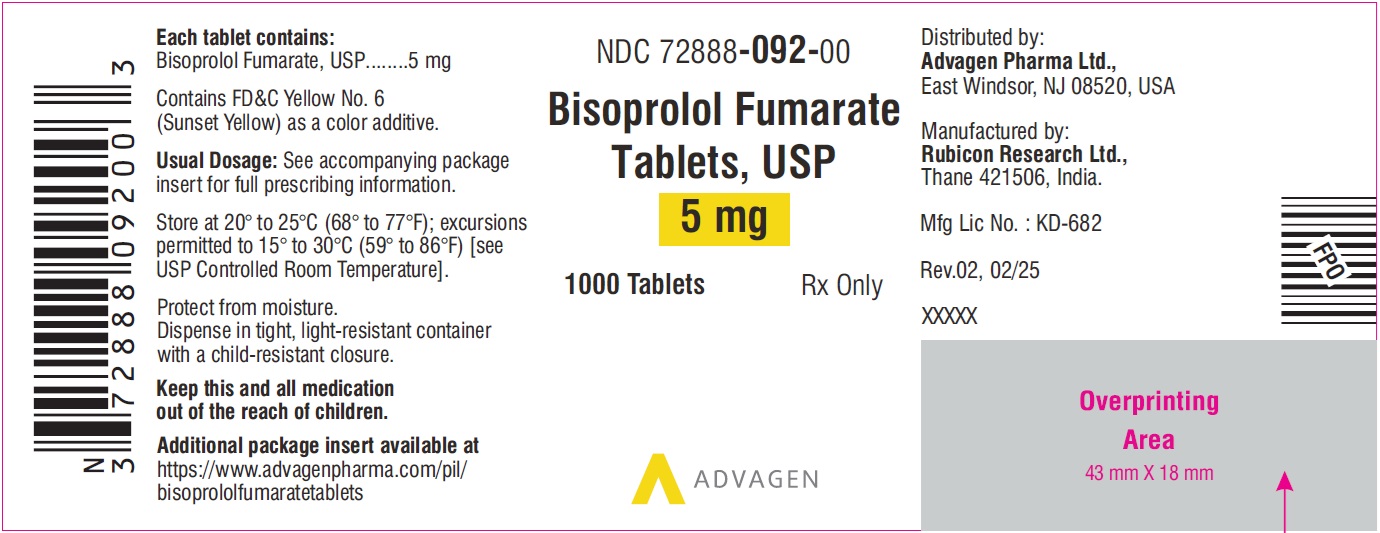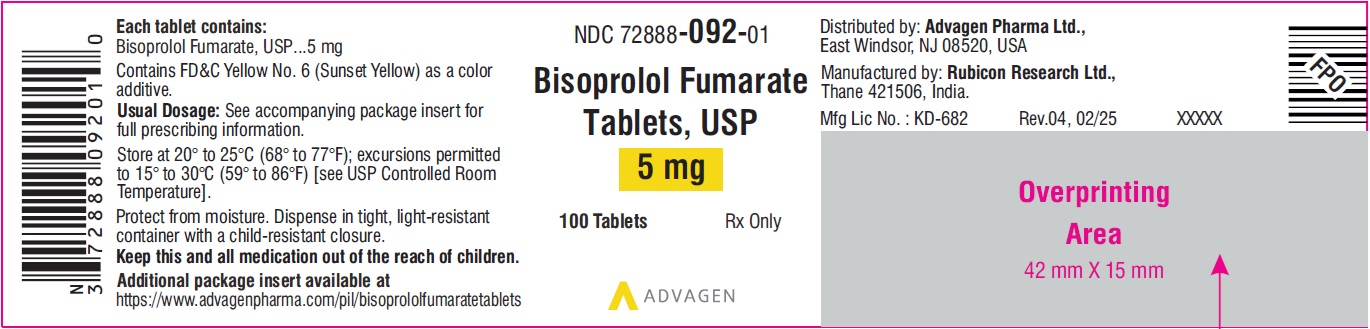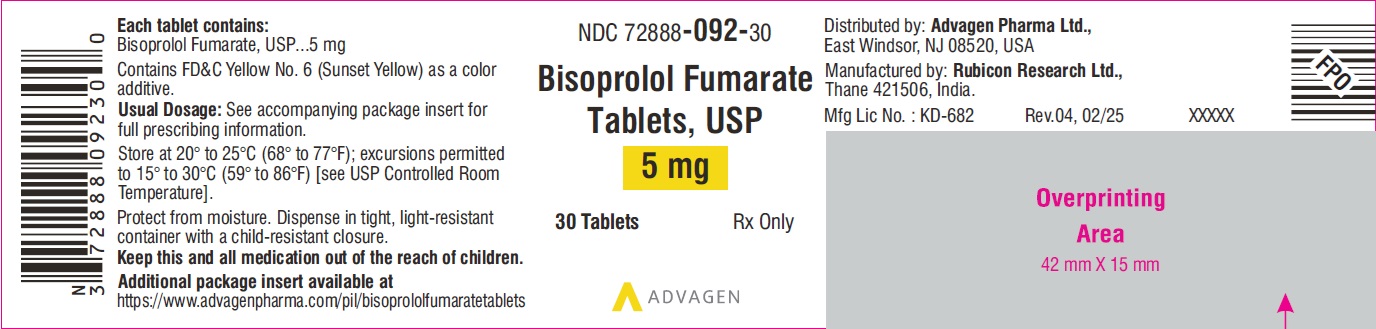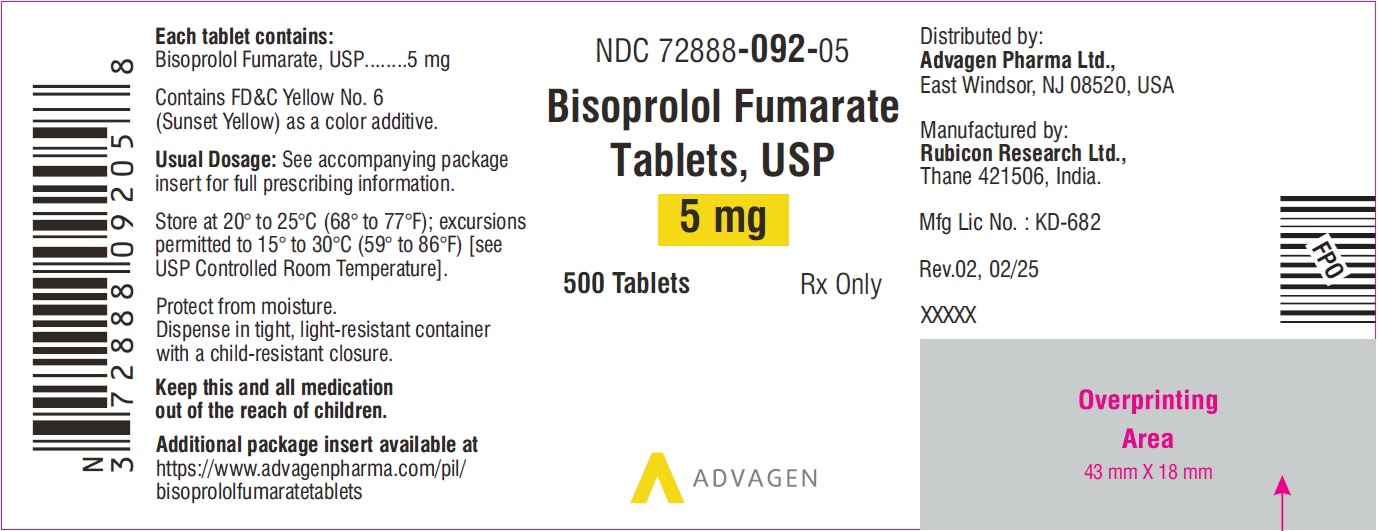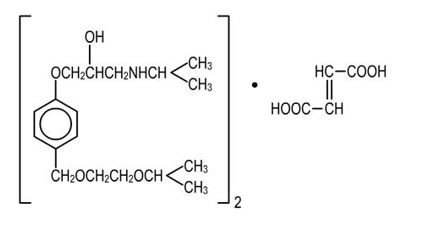 DRUG LABEL: Bisoprolol Fumarate
NDC: 72888-233 | Form: TABLET, FILM COATED
Manufacturer: Advagen Pharma Ltd
Category: prescription | Type: HUMAN PRESCRIPTION DRUG LABEL
Date: 20251112

ACTIVE INGREDIENTS: BISOPROLOL FUMARATE 2.5 mg/1 1
INACTIVE INGREDIENTS: SILICON DIOXIDE; STARCH, CORN; ANHYDROUS DIBASIC CALCIUM PHOSPHATE; HYPROMELLOSE, UNSPECIFIED; MAGNESIUM STEARATE; MICROCRYSTALLINE CELLULOSE; POLYETHYLENE GLYCOL, UNSPECIFIED; POLYSORBATE 80; TITANIUM DIOXIDE

Bisoprolol Fumarate Tablets, USP 2.5 mg, 5 mg and 10 mg

DESCRIPTION

Bisoprolol fumarate is a synthetic, beta1-selective (cardioselective) adrenoceptor blocking agent. The chemical name for bisoprolol fumarate is (±)-1-[4-[[2-(1-Methylethoxy)ethoxy]methyl]phenoxy]-3-[(1-methylethyl)amino]-2-propanol(E)-2-butenedioate (2:1) (salt). It possesses an asymmetric carbon atom in its structure and is provided as a racemic mixture. The S(-) enantiomer is responsible for most of the beta-blocking activity. Its empirical formula is (C18H31NO4)2•C4H4O4and its structure is:

Bisoprolol fumarate has a molecular weight of 766.97. It is a white crystalline powder which is approximately equally hydrophilic and lipophilic, and is readily soluble in water, methanol, ethanol, and chloroform.
Bisoprolol fumarate tablets, USP are available as 2.5 mg, 5 mg and 10 mg tablets for oral administration.
Inactive ingredients include Colloidal Silicon Dioxide, Corn Starch, Dibasic Calcium Phosphate, Hypromellose, Magnesium Stearate, Microcrystalline Cellulose, Polyethylene Glycol, Polysorbate 80, and Titanium Dioxide. The 5 mg tablets also contain FD&C Red # 40/Allura Red AC aluminum lake, FD&C Yellow # 6/Sunset Yellow FCF aluminum lake.

FDA approved dissolution test specifications differ from USP.

CLINICAL PHARMACOLOGY

Bisoprolol fumarate is a beta1-selective (cardioselective) adrenoceptor blocking agent without significant membrane stabilizing activity or intrinsic sympathomimetic activity in its therapeutic dosage range. Cardioselectivity is not absolute, however, and at higher doses (≥ 20 mg) bisoprolol fumarate also inhibits beta2-adrenoceptors, chiefly located in the bronchial and vascular musculature; to retain selectivity it is therefore important to use the lowest effective dose.
Pharmacokinetics and Metabolism
The absolute bioavailability after a 10 mg oral dose of bisoprolol fumarate is about 80%. Absorption is not affected by the presence of food. The first pass metabolism of bisoprolol fumarate is about 20%.
Binding to serum proteins is approximately 30%. Peak plasma concentrations occur within 2-4 hours of dosing with 5 to 20 mg, and mean peak values range from 16 ng/mL at 5 mg to 70 ng/mL at 20 mg. Once daily dosing with bisoprolol fumarate results in less than twofold intersubject variation in peak plasma levels. The plasma elimination half-life is 9-12 hours and is slightly longer in elderly patients, in part because of decreased renal function in that population. Steady state is attained within 5 days of once daily dosing. In both young and elderly populations, plasma accumulation is low; the accumulation factor ranges from 1.1 to 1.3, and is what would be expected from the first order kinetics and once daily dosing. Plasma concentrations are proportional to the administered dose in the range of 5 to 20 mg. Pharmacokinetic characteristics of the two enantiomers are similar.
Bisoprolol fumarate is eliminated equally by renal and non-renal pathways with about 50% of the dose appearing unchanged in the urine and the remainder appearing in the form of inactive metabolites. In humans, the known metabolites are labile or have no known pharmacologic activity. Less than 2% of the dose is excreted in the feces. Bisoprolol fumarate is not metabolized by cytochrome P450 II D6 (debrisoquin hydroxylase).
In subjects with creatinine clearance less than 40 mL/min, the plasma half-life is increased approximately threefold compared to healthy subjects.
In patients with cirrhosis of the liver, the elimination of bisoprolol fumarate is more variable in rate and significantly slower than that in healthy subjects, with plasma half-life ranging from 8.3 to 21.7 hours.
Pharmacodynamics
The most prominent effect of bisoprolol fumarate is the negative chronotropic effect, resulting in a reduction in resting and exercise heart rate. There is a fall in resting and exercise cardiac output with little observed change in stroke volume, and only a small increase in right atrial pressure, or pulmonary capillary wedge pressure at rest or during exercise.
Findings in short-term clinical hemodynamics studies with bisoprolol fumarate are similar to those observed with other beta-blocking agents.
The mechanism of action of its antihypertensive effects has not been completely established. Factors which may be involved include:
1) Decreased cardiac output,
2) Inhibition of renin release by the kidneys,
3) Diminution of tonic sympathetic outflow from the vasomotor centers in the brain.
In normal volunteers, bisoprolol fumarate therapy resulted in a reduction of exercise- and isoproterenol-induced tachycardia. The maximal effect occurred within 1-4 hours post-dosing. Effects persisted for 24 hours at doses equal to or greater than 5 mg.
Electrophysiology studies in man have demonstrated that bisoprolol fumarate significantly decreases heart rate, increases sinus node recovery time, prolongs AV node refractory periods, and, with rapid atrial stimulation, prolongs AV nodal conduction.
Beta1-selectivity of bisoprolol fumarate has been demonstrated in both animal and human studies. No effects at therapeutic doses on beta2-adrenoceptor density have been observed. Pulmonary function studies have been conducted in healthy volunteers, asthmatics, and patients with chronic obstructive pulmonary disease (COPD). Doses of bisoprolol fumarate ranged from 5 to 60 mg, atenolol from 50 to 200 mg, metoprolol from 100 to 200 mg, and propranolol from 40 to 80 mg. In some studies, slight, asymptomatic increases in airways resistance (AWR) and decreases in forced expiratory volume (FEV1) were observed with doses of bisoprolol fumarate 20 mg and higher, similar to the small increases in AWR also noted with the other cardioselective beta-blockers. The changes induced by beta-blockade with all agents were reversed by bronchodilator therapy.
Bisoprolol fumarate had minimal effect on serum lipids during antihypertensive studies. In U.S. placebo-controlled trials, changes in total cholesterol averaged +0.8% for bisoprolol fumarate-treated patients, and +0.7% for placebo. Changes in triglycerides averaged +19% for bisoprolol fumarate-treated patients, and +17% for placebo.
Bisoprolol fumarate has also been given concomitantly with thiazide diuretics. Even very low doses of hydrochlorothiazide (6.25 mg) were found to be additive with bisoprolol fumarate in lowering blood pressure in patients with mild-to-moderate hypertension.
CLINICAL STUDIES
In two randomized double-blind placebo-controlled trials conducted in the U.S., reductions in systolic and diastolic blood pressure and heart rate 24 hours after dosing in patients with mild-to-moderate hypertension are shown below. In both studies, mean systolic/diastolic blood pressures at baseline were approximately 150/100 mm Hg, and mean heart rate was 76 bpm. Drug effect is calculated by subtracting the placebo effect from the overall change in blood pressure and heart rate.

Sitting Systolic/Diastolic Pressure (BP) and Heart Rate (HR)
Mean Decrease (D) After 3 to 4 Weeks

Study A | Bisoprolol Fumarate
 | Placebo | 5 mg | 10 mg | 20 mg
n= | 61 | 61 | 61 | 61
Total ΔBP (mm Hg) | 5.4/3.2 | 10.4/8.0 | 11.2/10.9 | 12.8/11.9
Drug Effecta | - | 5.0/4.8 | 5.8/7.7 | 7.4/8.7
Total ΔHR (bpm) | 0.5 | 7.2 | 8.7 | 11.3
Drug Effecta | - | 6.7 | 8.2 | 10.8
Study B | Bisoprolol Fumarate
 | Placebo | 2.5 mg | 10 mg
n= | 56 | 59 | 62
Total ΔBP (mm Hg) | 3.0/3.7 | 7.6/8.1 | 13.5/11.2
Drug Effecta | - | 4.6/4.4 | 10.5/7.5
Total ΔHR (bpm) | 1.6 | 3.8 | 10.7
Drug Effecta | - | 2.2 | 9.1
aObserved total change from baseline minus placebo.

Blood pressure responses were seen within one week of treatment and changed little thereafter. They were sustained for 12 weeks and for over a year in studies of longer duration. Blood pressure returned to baseline when bisoprolol fumarate was tapered over two weeks in a long-term study.
Overall, significantly greater blood pressure reductions were observed on bisoprolol fumarate than on placebo regardless of race, age, or gender. There were no significant differences in response between black and nonblack patients.

INDICATIONS AND USAGE

Bisoprolol fumarate tablets are indicated in the management of hypertension. It may be used alone or in combination with other antihypertensive agents.

CONTRAINDICATIONS

Bisoprolol fumarate is contraindicated in patients with cardiogenic shock, overt cardiac failure, second or third degree AV block, and marked sinus bradycardia.

WARNINGS

Cardiac Failure
Sympathetic stimulation is a vital component supporting circulatory function in the setting of congestive heart failure, and beta-blockade may result in further depression of myocardial contractility and precipitate more severe failure. In general, beta-blocking agents should be avoided in patients with overt congestive failure. However, in some patients with compensated cardiac failure it may be necessary to utilize them. In such a situation, they must be used cautiously.
In Patients Without a History of Cardiac Failure
Continued depression of the myocardium with beta-blockers can, in some patients, precipitate cardiac failure. At the first signs or symptoms of heart failure, discontinuation of bisoprolol fumarate should be considered. In some cases, beta-blocker therapy can be continued while heart failure is treated with other drugs.
Abrupt Cessation of Therapy
Exacerbation of angina pectoris, and, in some instances, myocardial infarction or ventricular arrhythmia, have been observed in patients with coronary artery disease following abrupt cessation of therapy with beta-blockers. Such patients should, therefore, be cautioned against interruption or discontinuation of therapy without the physician's advice. Even in patients without overt coronary artery disease, it may be advisable to taper therapy with bisoprolol fumarate over approximately one week with the patient under careful observation. If withdrawal symptoms occur, bisoprolol fumarate therapy should be reinstituted, at least temporarily.
Peripheral Vascular Disease
Beta-blockers can precipitate or aggravate symptoms of arterial insufficiency in patients with peripheral vascular disease. Caution should be exercised in such individuals.

Bronchospastic Disease

PATIENTS WITH BRONCHOSPASTIC DISEASE SHOULD, IN GENERAL, NOT RECEIVE BETA-BLOCKERS. Because of its relative beta1-selectivity, however, bisoprolol fumarate may be used with caution in patients with bronchospastic disease who do not respond to, or who cannot tolerate other antihypertensive treatment. Since beta1-selectivity is not absolute, the lowest possible dose of bisoprolol fumarate should be used, with therapy starting at 2.5 mg. A beta2agonist (bronchodilator) should be made available.
Major Surgery
Chronically administered beta-blocking therapy should not be routinely withdrawn prior to major surgery; however, the impaired ability of the heart to respond to reflex adrenergic stimuli may augment the risks of general anesthesia and surgical procedures.
Diabetes and Hypoglycemia
Beta-blockers may mask some of the manifestations of hypoglycemia, particularly tachycardia. Nonselective beta-blockers may potentiate insulin-induced hypoglycemia and delay recovery of serum glucose levels. Because of its beta1-selectivity, this is less likely with bisoprolol fumarate. However, patients subject to spontaneous hypoglycemia, or diabetic patients receiving insulin or oral hypoglycemic agents, should be cautioned about these possibilities and bisoprolol fumarate should be used with caution.
Thyrotoxicosis
Beta-adrenergic blockade may mask clinical signs of hyperthyroidism, such as tachycardia. Abrupt withdrawal of beta-blockade may be followed by an exacerbation of the symptoms of hyperthyroidism or may precipitate thyroid storm.

PRECAUTIONS

Impaired Renal or Hepatic Function
Use caution in adjusting the dose of bisoprolol fumarate in patients with renal or hepatic impairment (see CLINICAL PHARMACOLOGYand DOSAGE AND ADMINISTRATION).
Drug Interactions
Bisoprolol fumarate should not be combined with other beta-blocking agents. Patients receiving catecholamine-depleting drugs, such as reserpine or guanethidine, should be closely monitored, because the added beta-adrenergic blocking action of bisoprolol fumarate may produce excessive reduction of sympathetic activity. In patients receiving concurrent therapy with clonidine, if therapy is to be discontinued, it is suggested that bisoprolol fumarate be discontinued for several days before the withdrawal of clonidine.
Bisoprolol fumarate should be used with care when myocardial depressants or inhibitors of AV conduction, such as certain calcium antagonists (particularly of the phenylalkylamine [verapamil] and benzothiazepine [diltiazem] classes), or antiarrhythmic agents, such as disopyramide, are used concurrently.
Both digitalis glycosides and beta-blockers slow atrioventricular conduction and decrease heart rate. Concomitant use can increase the risk of bradycardia.
Concurrent use of rifampin increases the metabolic clearance of bisoprolol fumarate, resulting in a shortened elimination half-life of bisoprolol fumarate. However, initial dose modification is generally not necessary. Pharmacokinetic studies document no clinically relevant interactions with other agents given concomitantly, including thiazide diuretics and cimetidine. There was no effect of bisoprolol fumarate on prothrombin time in patients on stable doses of warfarin.
Risk of Anaphylactic Reaction:
While taking beta-blockers, patients with a history of severe anaphylactic reaction to a variety of allergens may be more reactive to repeated challenge, either accidental, diagnostic, or therapeutic. Such patients may be unresponsive to the usual doses of epinephrine used to treat allergic reactions.

Information for Patients

Patients, especially those with coronary artery disease, should be warned about discontinuing use of bisoprolol fumarate without a physician's supervision. Patients should also be advised to consult a physician if any difficulty in breathing occurs, or if they develop signs or symptoms of congestive heart failure or excessive bradycardia.
Patients subject to spontaneous hypoglycemia, or diabetic patients receiving insulin or oral hypoglycemic agents, should be cautioned that beta-blockers may mask some of the manifestations of hypoglycemia, particularly tachycardia, and bisoprolol fumarate should be used with caution.
Patients should know how they react to this medicine before they operate automobiles and machinery or engage in other tasks requiring alertness.

Carcinogenesis, Mutagenesis, Impairment of Fertility

Long-term studies were conducted with oral bisoprolol fumarate administered in the feed of mice (20 and 24 months) and rats (26 months). No evidence of carcinogenic potential was seen in mice dosed up to 250 mg/kg/day or rats dosed up to 125 mg/kg/day. On a body weight basis, these doses are 625 and 312 times, respectively, the maximum recommended human dose (MRHD) of 20 mg, (or 0.4 mg/kg/day based on a 50 kg individual); on a body surface area basis, these doses are 59 times (mice) and 64 times (rats) the MRHD. The mutagenic potential of bisoprolol fumarate was evaluated in the microbial mutagenicity (Ames) test, the point mutation and chromosome aberration assays in Chinese hamster V79 cells, the unscheduled DNA synthesis test, the micronucleus test in mice, and the cytogenetics assay in rats. There was no evidence of mutagenic potential in these in vitroand in vivoassays.
Reproduction studies in rats did not show any impairment of fertility at doses up to 150 mg/kg/day of bisoprolol fumarate, or 375 and 77 times the MRHD on the basis of body weight and body surface area, respectively.

Nursing Mothers

Small amounts of bisoprolol fumarate (< 2% of the dose) have been detected in the milk of lactating rats. It is not known whether this drug is excreted in human milk. Because many drugs are excreted in human milk caution should be exercised when bisoprolol fumarate is administered to nursing women.

Pediatric Use

Safety and effectiveness in pediatric patients have not been established.

Geriatric Use

Bisoprolol fumarate has been used in elderly patients with hypertension. Response rates and mean decreases in systolic and diastolic blood pressure were similar to the decreases in younger patients in the U.S. clinical studies. Although no dose response study was conducted in elderly patients, there was a tendency for older patients to be maintained on higher doses of bisoprolol fumarate.
Observed reductions in heart rate were slightly greater in the elderly than in the young and tended to increase with increasing dose. In general, no disparity in adverse experience reports or dropouts for safety reasons was observed between older and younger patients. Dose adjustment based on age is not necessary.

ADVERSE REACTIONS

Safety data are available in more than 30,000 patients or volunteers. Frequency estimates and rates of withdrawal of therapy for adverse events were derived from two U.S. placebo-controlled studies.
In Study A, doses of 5, 10, and 20 mg bisoprolol fumarate were administered for 4 weeks. In Study B, doses of 2.5, 10, and 40 mg of bisoprolol fumarate were administered for 12 weeks. A total of 273 patients were treated with 5-20 mg of bisoprolol fumarate; 132 received placebo.
Withdrawal of therapy for adverse events was 3.3% for patients receiving bisoprolol fumarate and 6.8% for patients on placebo. Withdrawals were less than 1% for either bradycardia or fatigue/lack of energy.
The following table presents adverse experiences, whether or not considered drug related, reported in at least 1% of patients in these studies, for all patients studied in placebo-controlled clinical trials (2.5-40 mg), as well as for a subgroup that was treated with doses within the recommended dosage range (5-20 mg). Of the adverse events listed in the table, bradycardia, diarrhea, asthenia, fatigue, and sinusitis appear to be dose related.

Body System/Adverse Experience | All Adverse Experiences (%a) Bisoprolol Fumarate
Body System/Adverse Experience | Placebo (n=132) % | 5-20 mg (n=273) % | 2.5-40 mg (n=404) %
Skin
increased sweating | 1.5 | 0.7 | 1.0
Musculoskeletal
arthralgia | 2.3 | 2.2 | 2.7
Central Nervous System
dizziness | 3.8 | 2.9 | 3.5
headache | 11.4 | 8.8 | 10.9
hypoaesthesia | 0.8 | 1.1 | 1.5
Autonomic Nervous System
dry mouth | 1.5 | 0.7 | 1.3
Heart Rate/Rhythm
bradycardia | 0 | 0.4 | 0.5
Psychiatric
vivid dreams | 0 | 0 | 0
insomnia | 2.3 | 1.5 | 2.5
depression | 0.8 | 0 | 0.2
Gastrointestinal
diarrhea | 1.5 | 2.6 | 3.5
nausea | 1.5 | 1.5 | 2.2
vomiting | 0 | 1.1 | 1.5
Respiratory
bronchospasm | 0 | 0 | 0
cough | 4.5 | 2.6 | 2.5
dyspnea | 0.8 | 1.1 | 1.5
pharyngitis | 2.3 | 2.2 | 2.2
rhinitis | 3.0 | 2.9 | 4.0
sinusitis | 1.5 | 2.2 | 2.2
URI | 3.8 | 4.8 | 5.0
Body as a Whole
asthenia | 0 | 0.4 | 1.5
chest pain | 0.8 | 1.1 | 1.5
fatigue | 1.5 | 6.6 | 8.2
edema (peripheral) | 3.8 | 3.7 | 3.0
apercentage of patients with event

The following is a comprehensive list of adverse experiences reported with bisoprolol fumarate in worldwide studies, or in postmarketing experience (in italics):
Central Nervous System
Dizziness, unsteadiness, vertigo, syncope, headache, paresthesia, hypoesthesia, hyperesthesia, somnolence, sleep disturbances, anxiety/restlessness, decreased concentration/memory.
Autonomic Nervous System
Dry mouth.
Cardiovascular
Bradycardia, palpitations and other rhythm disturbances, cold extremities, claudication, hypotension, orthostatic hypotension, chest pain, congestive heart failure, dyspnea on exertion.
Psychiatric
Vivid dreams, insomnia, depression.
Gastrointestinal
Gastric/epigastric/abdominal pain, gastritis, dyspepsia, nausea, vomiting, diarrhea, constipation, peptic ulcer.
Musculoskeletal
Muscle/joint pain, arthralgia, back/neck pain, muscle cramps, twitching/tremor.
Skin
Rash, acne, eczema, psoriasis, skin irritation, pruritus, flushing, sweating, alopecia, dermatitis, angioedema, exfoliative dermatitis,cutaneous vasculitis.
Special Senses
Visual disturbances, ocular pain/pressure, abnormal lacrimation, tinnitus, decreased hearing, earache, taste abnormalities.
Metabolic
Gout.
Respiratory
Asthma/bronchospasm, bronchitis, coughing, dyspnea, pharyngitis, rhinitis, sinusitis, URI.
Genitourinary
Decreased libido/impotence, Peyronie's disease,cystitis, renal colic, polyuria.
Hematologic
Purpura.
General
Fatigue, asthenia, chest pain, malaise, edema, weight gain, angioedema.
In addition, a variety of adverse effects have been reported with other beta-adrenergic blocking agents and should be considered potential adverse effects of bisoprolol fumarate.
Central Nervous System
Reversible mental depression progressing to catatonia, hallucinations, an acute reversible syndrome characterized by disorientation to time and place, emotional lability, slightly clouded sensorium.
Allergic
Fever, combined with aching and sore throat, laryngospasm, respiratory distress.
Hematologic
Agranulocytosis, thrombocytopenia, thrombocytopenic purpura.
Gastrointestinal
Mesenteric arterial thrombosis, ischemic colitis.
Miscellaneous
The oculomucocutaneous syndrome associated with the beta-blocker practolol has not been reported with bisoprolol fumarate during investigational use or extensive foreign marketing experience.
LABORATORY ABNORMALITIES
In clinical trials, the most frequently reported laboratory change was an increase in serum triglycerides, but this was not a consistent finding.
Sporadic liver test abnormalities have been reported. In the U.S. controlled trials experience with bisoprolol fumarate treatment for 4-12 weeks, the incidence of concomitant elevations in SGOT and SGPT from 1 to 2 times normal was 3.9%, compared to 2.5% for placebo. No patient had concomitant elevations greater than twice normal.
In the long-term, uncontrolled experience with bisoprolol fumarate treatment for 6-18 months, the incidence of one or more concomitant elevations in SGOT and SGPT from 1 to 2 times normal was 6.2%. The incidence of multiple occurrences was 1.9%. For concomitant elevations in SGOT and SGPT of greater than twice normal, the incidence was 1.5%. The incidence of multiple occurrences was 0.3%. In many cases these elevations were attributed to underlying disorders, or resolved during continued treatment with bisoprolol fumarate.
Other laboratory changes included small increases in uric acid, creatinine, BUN, serum potassium, glucose, and phosphorus and decreases in WBC and platelets. These were generally not of clinical importance and rarely resulted in discontinuation of bisoprolol fumarate.
As with other beta-blockers, ANA conversions have also been reported on bisoprolol fumarate. About 15% of patients in long-term studies converted to a positive titer, although about one-third of these patients subsequently reconverted to a negative titer while on continued therapy.

OVERDOSAGE

The most common signs expected with overdosage of a beta-blocker are bradycardia, hypotension, congestive heart failure, bronchospasm, and hypoglycemia. To date, a few cases of overdose (maximum: 2000 mg) with bisoprolol fumarate have been reported. Bradycardia and/or hypotension were noted. Sympathomimetic agents were given in some cases, and all patients recovered.
In general, if overdose occurs, bisoprolol fumarate therapy should be stopped and supportive and symptomatic treatment should be provided. Limited data suggest that bisoprolol fumarate is not dialyzable. Based on the expected pharmacologic actions and recommendations for other beta-blockers, the following general measures should be considered when clinically warranted:
Bradycardia
Administer IV atropine. If the response is inadequate, isoproterenol or another agent with positive chronotropic properties may be given cautiously. Under some circumstances, transvenous pacemaker insertion may be necessary.
Hypotension
IV fluids and vasopressors should be administered. Intravenous glucagon may be useful.
Heart Block (second or third degree)
Patients should be carefully monitored and treated with isoproterenol infusion or transvenous cardiac pacemaker insertion, as appropriate.
Congestive Heart Failure
Initiate conventional therapy (ie, digitalis, diuretics, inotropic agents, vasodilating agents).
Bronchospasm
Administer bronchodilator therapy such as isoproterenol and/or aminophylline.
Hypoglycemia
Administer IV glucose.

DOSAGE AND ADMINISTRATION

The dose of bisoprolol fumarate tablets must be individualized to the needs of the patient. The usual starting dose is 5 mg once daily. In some patients, 2.5 mg may be an appropriate starting dose (see Bronchospastic Diseasein WARNINGS). If the antihypertensive effect of 5 mg is inadequate, the dose may be increased to 10 mg and then, if necessary, to 20 mg once daily.
Patients with Renal or Hepatic Impairment
In patients with hepatic impairment (hepatitis or cirrhosis) or renal dysfunction (creatinine clearance less than 40 mL/min), the initial daily dose should be 2.5 mg and caution should be used in dose-titration. Since limited data suggest that bisoprolol fumarate is not dialyzable, drug replacement is not necessary in patients undergoing dialysis.
Geriatric Patients
It is not necessary to adjust the dose in the elderly, unless there is also significant renal or hepatic dysfunction (see above and Geriatric Usein PRECAUTIONS).
Pediatric Patients
There is no pediatric experience with bisoprolol fumarate tablets.

HOW SUPPLIED

Bisoprolol fumarate is supplied as 2.5 mg, 5 mg and 10 mg tablets.

The 2.5 mg tablets are White, round, coated tablets, plain on one side and debossed with ‘Λ’ on other side
H1
NDC 72888-233-01, bottles of 30
The 5 mg tablets are peach, round, coated tablets, scored on one side and debossed with ‘Λ’ on other side
F1

NDC 72888-092-30, bottles of 30
NDC 72888-092-01, bottles of 100
NDC 72888-092-05, bottles of 500
NDC 72888-092-00, bottles of 1000
The 10 mg tablets are white, round, coated tablets, plain on one side and debossed with ‘Λ’ on other side
F2
NDC 72888-093-30, bottles of 30
NDC 72888-093-01, bottles of 100
NDC 72888-093-05, bottles of 500
NDC 72888-093-00, bottles of 1000
Store at 20º to 25ºC (68º to 77ºF); excursions permitted to 15 º to 30ºC (59 º to 86ºF) [see USP Controlled Room Temperature]. Protect from moisture.
Dispense in tight containers.
Distributed by:

Advagen Pharma Ltd.
East Windsor, NJ, 08520, USA
Manufactured by:
Rubicon Research Limited
Thane, 421506,
INDIA
Rev.02, 02/2025

PACKAGE LABEL-PRINCIPAL DISPLAY PANEL

Bisoprolol Fumarate Tablets 2.5 mg - NDC 72888-233-01 - 30 Tablets Label

Bisoprolol Fumarate Tablets 5 mg - NDC 72888-092-30 - 30 Tablets Label

Bisoprolol Fumarate Tablets 5 mg - NDC 72888-092-01 - 100 Tablets Label

Bisoprolol Fumarate Tablets 5 mg - NDC 72888-092-05 - 500 Tablets Label

Bisoprolol Fumarate Tablets 5 mg - NDC 72888-092-00 - 1000 Tablets Label

Bisoprolol Fumarate Tablets 10 mg - NDC 72888-093-30 - 30 Tablets Label

Bisoprolol Fumarate Tablets 10 mg - NDC 72888-093-01 - 100 Tablets Label

Bisoprolol Fumarate Tablets 10 mg - NDC 72888-093-05 - 500 Tablets Label

Bisoprolol Fumarate Tablets 10 mg - NDC 72888-093-00 - 1000 Tablets Label